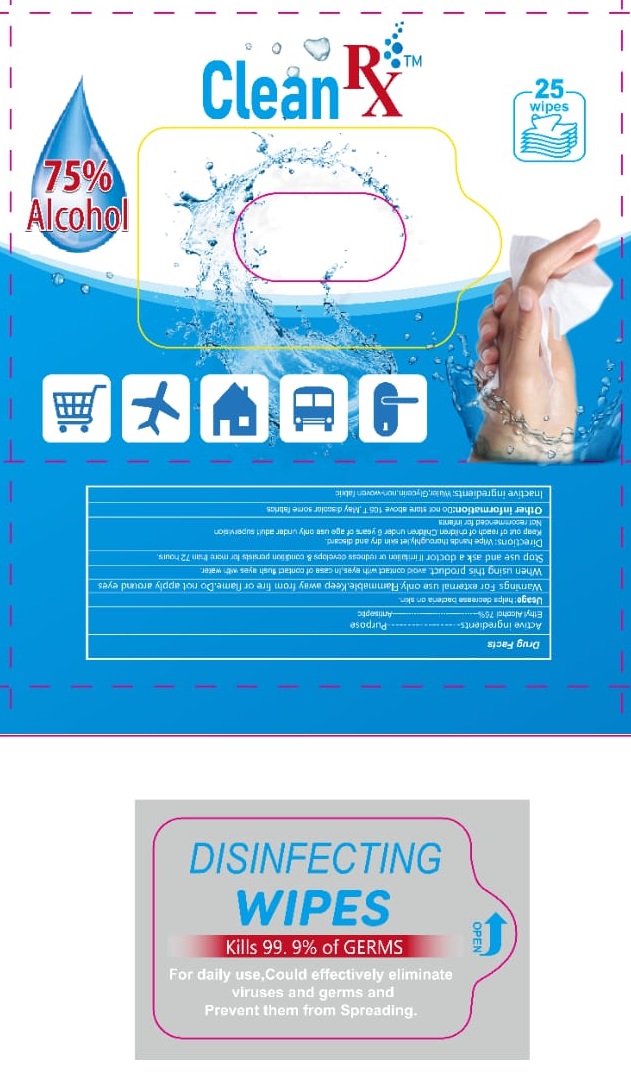 DRUG LABEL: Sanitizing Wipes
NDC: 76717-075 | Form: CLOTH
Manufacturer: Shenzhen spring cosmetics co.,LTD
Category: otc | Type: HUMAN OTC DRUG LABEL
Date: 20200604

ACTIVE INGREDIENTS: ALCOHOL 75 1/1 1
INACTIVE INGREDIENTS: GLYCERIN; WATER

Active Ingredient(s)

Ethyl Alcohol 75%

Purpose

Antiseptic

Use

Helps decrease bacteria on skin.

Warnings

For external use only. Flammable. Keep away from fire or flame.

Do not apply

around eyes

When using this product

avoid contact with eyes. In case of contact flush eyes with water.

Stop use and ask a doctor

If irritation or redness develops and condition persists for more than 72 hours.

Keep out of reach of children.

If swallowed, get medical help or contact a Poison Control Center right away. Children under 6 years of age use only under adult supervision.

Not recommended for infants

Directions

Wipe hands thoroughly, let skin dry and discard.

Other information

- Do not store above 106°F
- May discolor some fabrics

Inactive ingredients

Water, Glycerin, non woven fabric

Principal Display Panel

NDC: 76717-075-25

Clean RxTM

25 Wipes

75% Alcohol

DISINFECTING WIPES

KILLS 99.9% of GERMS

For daily use, Could effectively eliminate viruses and germs and Prevent them from spreading.